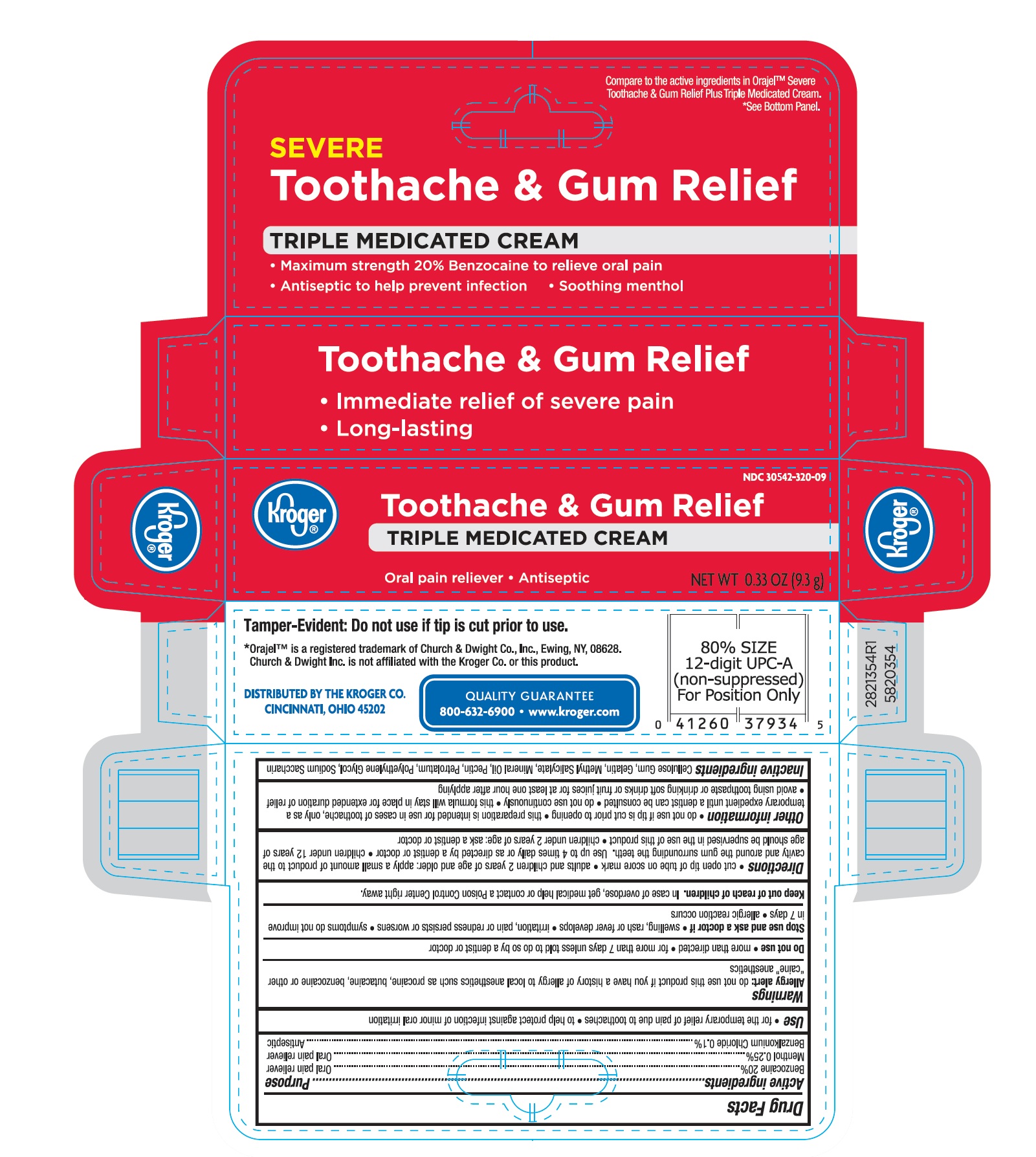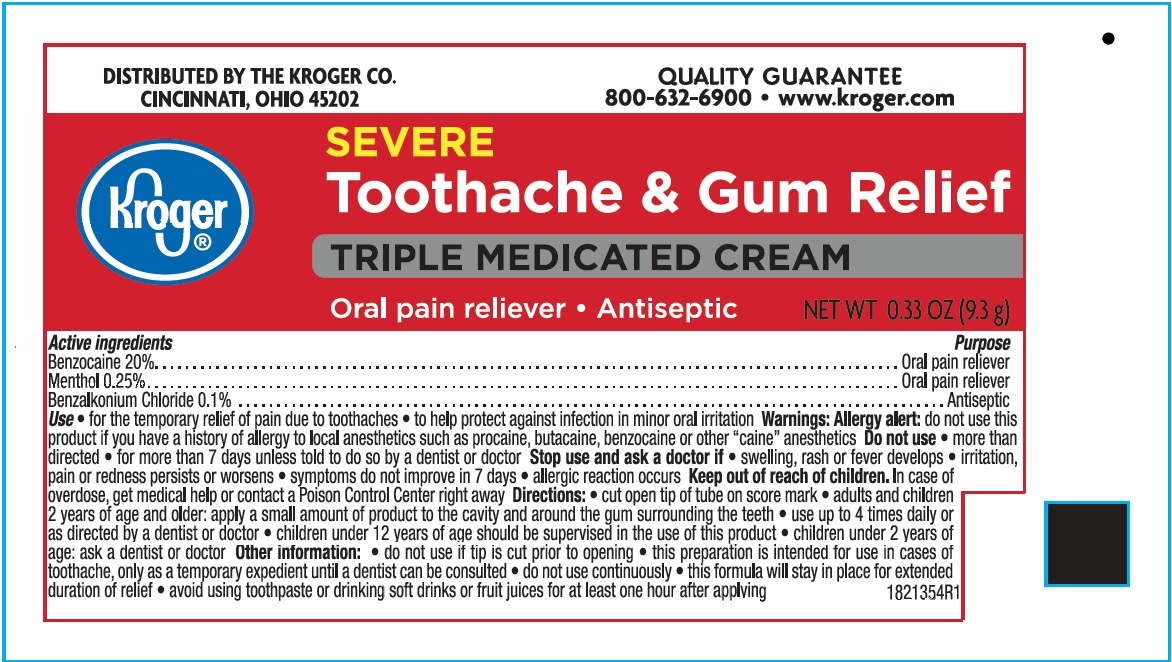 DRUG LABEL: Kroger
NDC: 30142-354 | Form: CREAM
Manufacturer: Kroger
Category: otc | Type: HUMAN OTC DRUG LABEL
Date: 20160729

ACTIVE INGREDIENTS: BENZOCAINE 20.00 g/100 g; MENTHOL 0.25 g/100 g
INACTIVE INGREDIENTS: BENZALKONIUM CHLORIDE 0.1 g/100 g; SACCHARIN SODIUM; PETROLATUM; MINERAL OIL; GELATIN; POLYETHYLENE GLYCOL 1000; METHYL SALICYLATE; PECTIN; Carboxymethylcellulose Sodium

Drug Facts

Active ingredient

Benzocaine 20.0% ..................................Oral pain reliever

Menthol 0.25% .......................................Oral pain reliever

Benzalkonium Chloride 0.1% ....................Antiseptic

Uses

for the temporary relief of pain due to toothaches

to help protect against infection of minor oral irritation

Allergy alert: do not use this product if you have a history of allergy to local anesthetics such as procaine, butacaine, benzocaine or other “caine” anesthetics

When using this product

- do not use more than directed
- for more than 7 days unless told to do so by a dentist or doctor

Stop use and ask a doctor if

- swelling rash or fever developes
- irritation, pain or redness persists or worsens
- symptoms do not improve in 7 days
- allergic reaction occurs

Keep out of reach of children. In case of overdose, get medical help or contact a Poison Control Center right away.

Directions

- cut open tip of tubne on score mark
- adults and children 2 years of age and older; apply a small amount of product to the cavity and arround the gum surrounding the teeth
- use up to 4 times daily or as directed by a dentist or doctor.
- Children under 12 years of age should be supervised in the use of this product.

Children under 2 years of age: ask a dentist or doctor.

Other Information

- do not use if tip is cut prior to opening
- this preparation is intended for use in cases of toothache, only as a temporary expedient until a dentist can be consulted
- do not use continuously
- this formula will stay in place for an extended duration of relief
- avoid using toothpaste or drinking softdrinks or fruit juices for at least one hour after applying

Inactive ingredients

Cellulose Gum, Gelatin, Methyl Salicylate, Mineral Oil, Pectin, Petrolatum, Polyethylene Glycol, Sodium Saccharin

DOSAGE AND ADMINISTRATION

Adults and children 2 years of age and older:
apply to affect4ed area using applicator tip
use up to 4 times daily or as directed by a dentist or doctor.
Children under 12 years of age should be supervised in the use of this product.
Children under 2 years of age: ask a dentist or doctor.